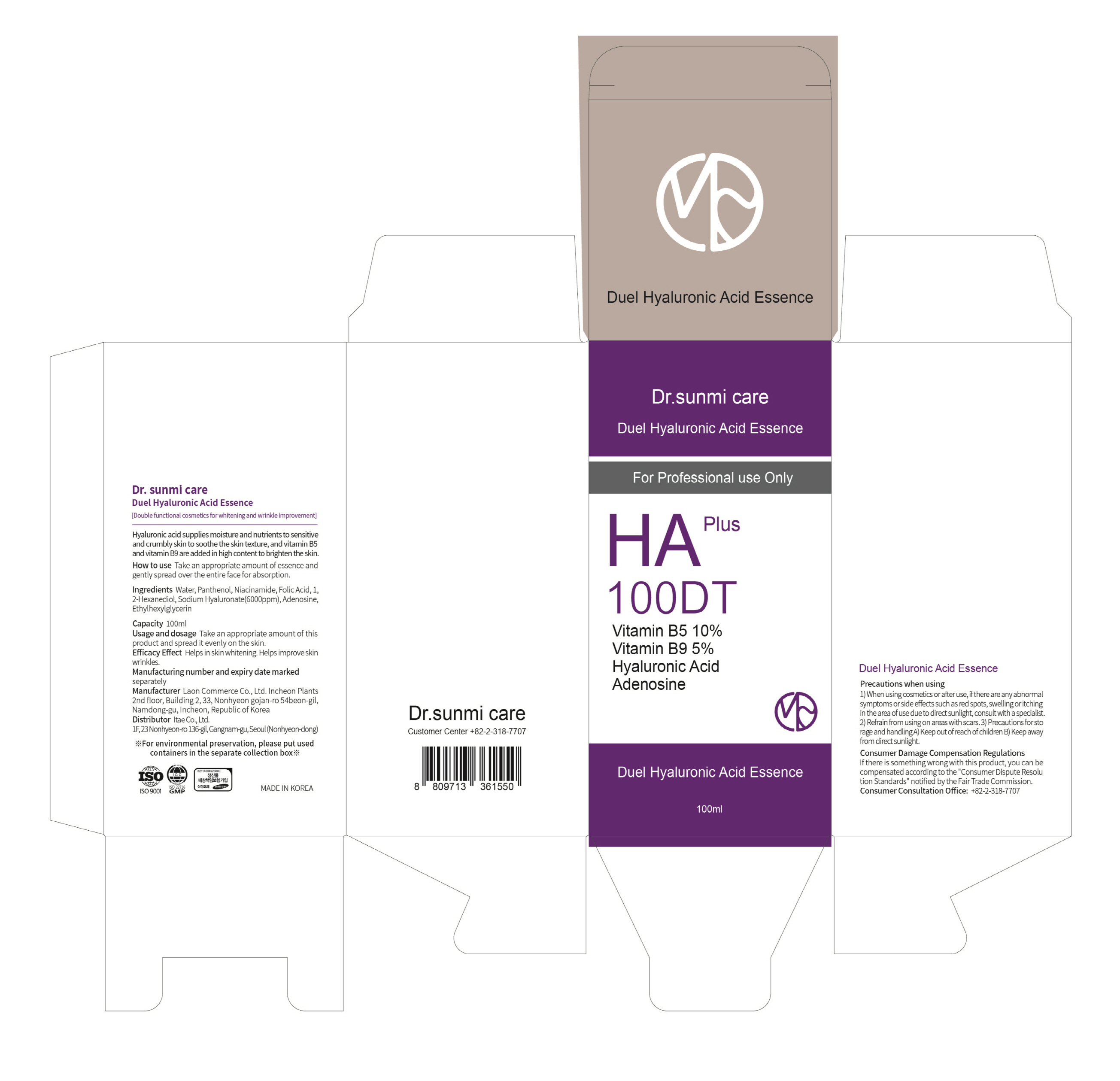 DRUG LABEL: Dr. sunmi care Duel Hyaluronic Acid Essence
NDC: 82083-0020 | Form: LIQUID
Manufacturer: LAON COMMERCE co ltd
Category: otc | Type: HUMAN OTC DRUG LABEL
Date: 20230627

ACTIVE INGREDIENTS: ADENOSINE 0.04 g/100 mL; NIACINAMIDE 5 g/100 mL
INACTIVE INGREDIENTS: WATER

ACTIVE INGREDIENT

Niacinamide, Adenosine

INACTIVE INGREDIENT

Water
Panthenol
Folic Acid
1,2-Hexanediol
Sodium Hyaluronate
Ethylhexylglycerin

PURPOSE

skin protect

KEEP OUT OF REACH OF THE CHILDREN

INDICATIONS AND USAGE

Take an appropriate amount of essence and gently spread over the entire face for absorption.

WARNINGS

2. Precautions when using

1) When using cosmetics or after use, if there are any abnormal

symptoms or side effects such as red spots, swelling or itching

in the area of u se due to direct sunlight, consult with a specialist.

2) Refrain from using on areas with scars. 3) Precautions for sto

rage and handling A) Keep out of reach of children B) Keep away

from direct sunlight.

DOSAGE AND ADMINISTRATION

topical use only